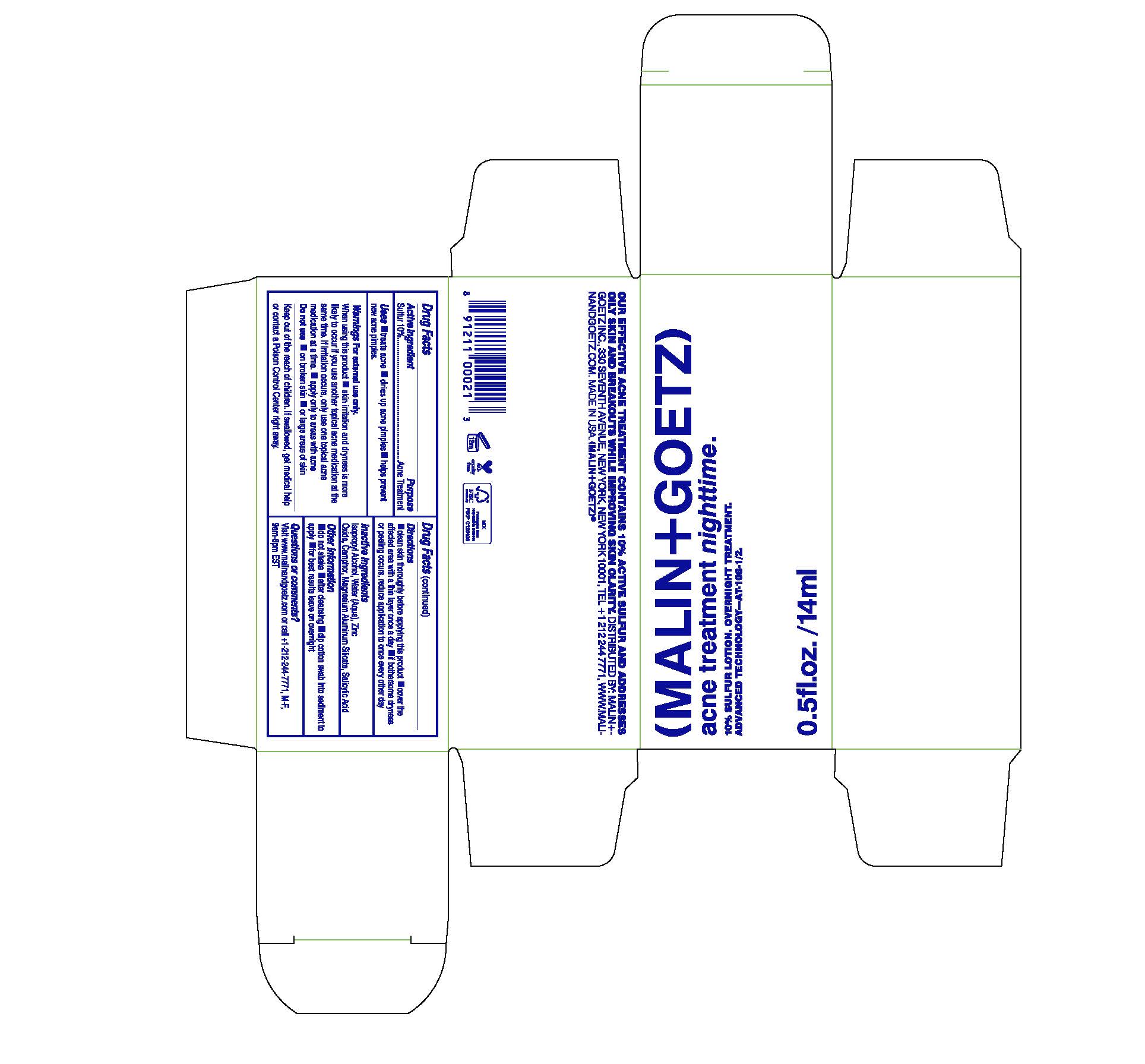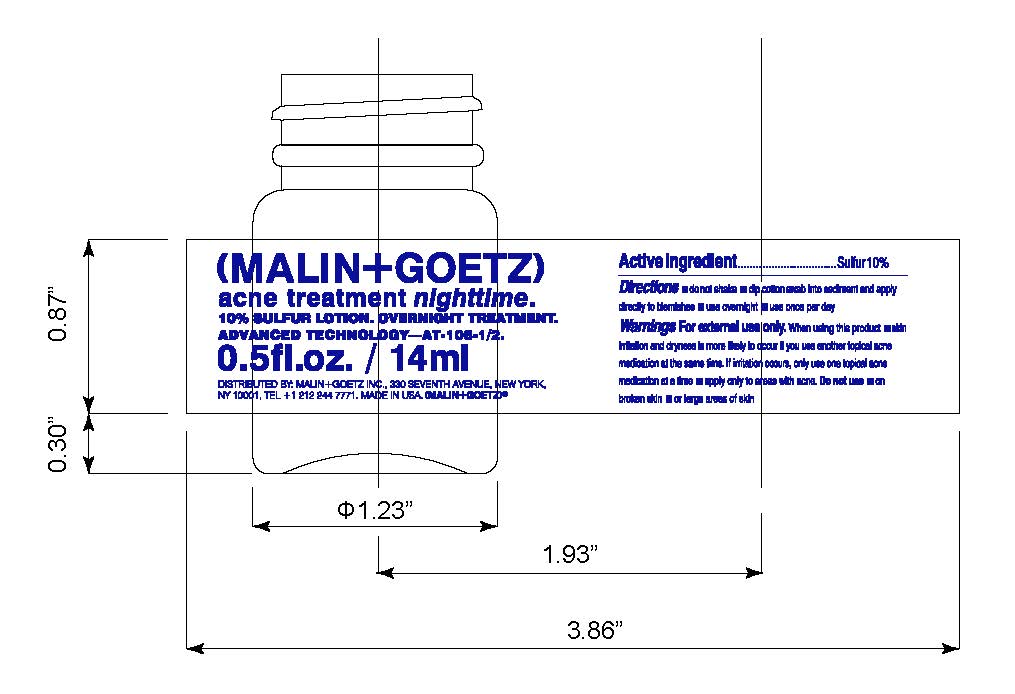 DRUG LABEL: Malin and Goetz
NDC: 53634-010 | Form: CREAM
Manufacturer: Malin and Goetz Inc
Category: otc | Type: HUMAN OTC DRUG LABEL
Date: 20251001

ACTIVE INGREDIENTS: SULFUR 10 g/100 mL
INACTIVE INGREDIENTS: ISOPROPYL ALCOHOL; WATER; ZINC OXIDE; CAMPHOR (SYNTHETIC); SALICYLIC ACID; MAGNESIUM ALUMINUM SILICATE

Acne treatment Nighttime

Active ingredient purpose

Sulfur 10% Acne Treatment

Uses

- treats acne
- dries up acne pimples
- helps prevent acne pimples

Keep out of reach of children. If swallowed, get medical help or contact a poison control center right away.

INDICATIONS AND USAGE

Skin irritation and dryness is more likely to occur if you use another topical acne medication at the same time. If irritation occurs, only use one topical acne medication at a time.

Warnings

For External Use only

When using this product

- apply only to areas with acne

Do not use

- on broken skin
- or large areas of skin

Directions

- Clean skin thoroughly before applying this product
- cover the affected area with a thin layer once a day
- if bothersome dryness or peeling occurs, reduce application to once every other day

Inactive Ingredients

Isopropyl Alcohol, Water, Zinc Oxide, Camphor, Salicylic Acid, Magnesium Aluminum Silicate

PACKAGE LABEL

(Malin + Goetz)

acne treatment nighttime

10% Sulfur lotion. Overnight Treatment

Advanced Technology

.5 fl. oz. 14ml